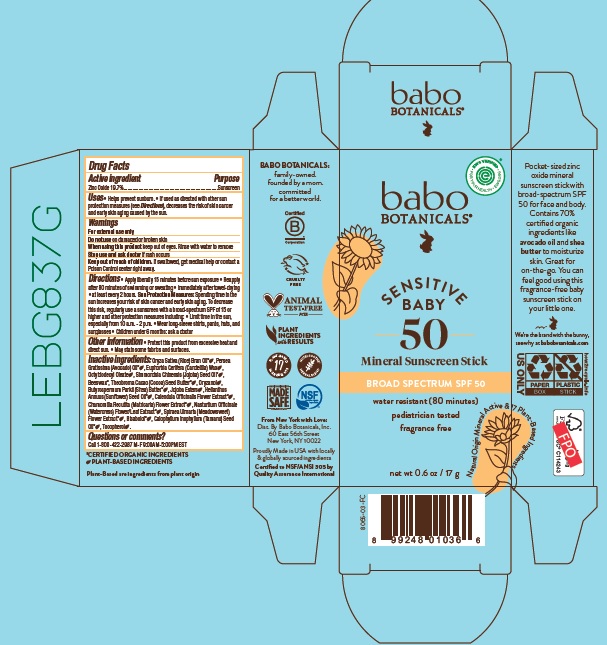 DRUG LABEL: Babo Botanicals Sensitive Baby Mineral Sunscreen SPF50
NDC: 79265-5608 | Form: STICK
Manufacturer: Babo Botanicals, Inc.
Category: otc | Type: HUMAN OTC DRUG LABEL
Date: 20231025

ACTIVE INGREDIENTS: ZINC OXIDE 197 mg/1 g
INACTIVE INGREDIENTS: TAMANU OIL; JOJOBA OIL; TOCOPHEROL; HYDROGENATED JOJOBA OIL, RANDOMIZED; ORYZANOL; WHITE WAX; CHAMOMILE; LEVOMENOL; CALENDULA OFFICINALIS FLOWER; CANDELILLA WAX; SHEA BUTTER; RICE BRAN OIL; OCTYLDODECYL OLEATE; FILIPENDULA ULMARIA FLOWER; COCOA BUTTER; CALOPHYLLUM TACAMAHACA SEED OIL; SUNFLOWER OIL; AVOCADO OIL; NASTURTIUM OFFICINALE FLOWERING TOP

Babo Botanicals Sensitive Baby Mineral Sunscreen SPF50

Active ingredient

Zinc Oxide 19.7%

Purpose

Sunscreen

Uses

- Helps prevent sunburn
- If used as directed with other sun protection measures (see Directions), decreases the risk of skin cancer and early skin aging caused by the sun.

Warnings

For external use only.

Do not use

on damaged or broken skin

When using this product

keep out of eyes. Rinse with water to remove

Stop use and ask a doctor

if rash occurs

Keep out of reach of children.

If swallowed, get medical help or contact a Poison Control center right away.

Directions

- Apply liberally 15 minutes before sun exposure.
- Reapply after 80 minutes of swimming or sweating
- immediately after towel-drying
- at least every 2 hours
- Sun Protection Measures. Spending time in the sun increases your risk of skin cancer and early skin aging. To decrease this risk, regularly use a sunscreen with a broad-spectrum SPF of 15 or higher and other protection measures including:
- Limit time in the sun, especially from 10 a.m. – 2 p.m.
- Wear long-sleeve shirts, pants, hats, and sunglasses
- Children under 6 months: ask a doctor

Other information

- Protect this product from excessive heat and direct sun.
- May stain some fabrics and surfaces.

Inactive ingredients

Oryza Sativa (Rice) Bran Oil*, Persea Gratissima (Avocado) Oil*, Euphorbia Cerifera (Candelilla) Wax, Octyldodecyl Oleate, Simmondsia Chinensis (Jojoba) Seed Oil*, Beeswax*, Theobroma Cacao (Cocoa) Seed Butter*, Oryzanol, Butyrospermum Parkii (Shea) Butter*, Jojoba Esters, Helianthus Annuus (Sunflower) Seed Oil*, Calendula Officinalis Flower Extract*, Chamomilla Recutita (Matricaria) Flower Extract*, Nasturtium Officinale (Watercress) Flower/Leaf Extract*, Spiraea Ulmaria (Meadowsweet) Flower Extract*, Bisabolol*, Calophyllum Inophyllum (Tamanu) Seed Oil*, Tocopherol.

*Certified Organic Ingredients

Company Information

Dist: by Babo Botanicals, Inc.
60 East 56th Street New York, NY 10022